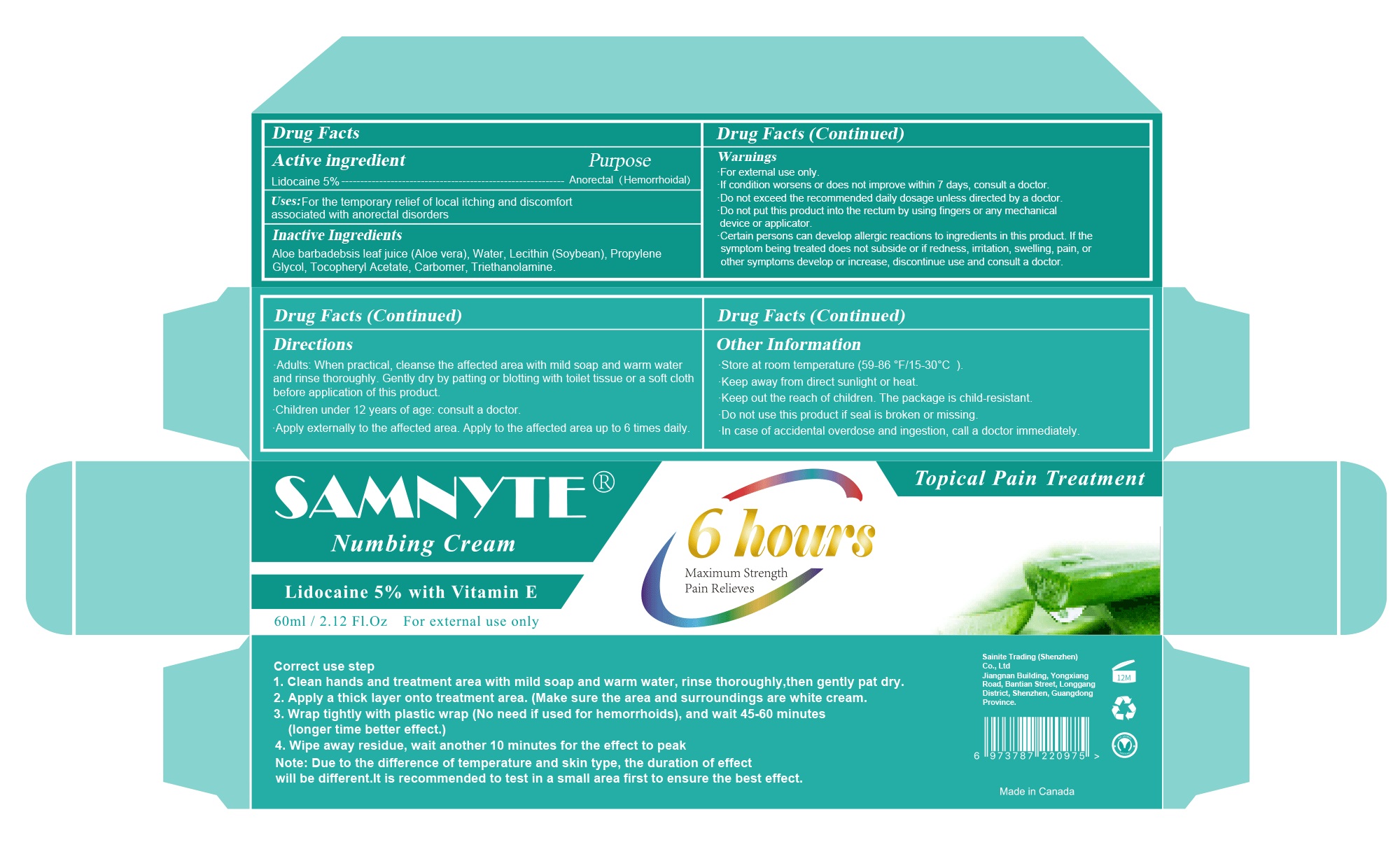 DRUG LABEL: Numbing Cream
NDC: 82929-011 | Form: EMULSION
Manufacturer: Sainite Trading Shenzhen Co., Ltd.
Category: otc | Type: HUMAN OTC DRUG LABEL
Date: 20260204

ACTIVE INGREDIENTS: LIDOCAINE 5 g/100 mL
INACTIVE INGREDIENTS: CARBOMER; ALOE BARBADENSIS LEAF JUICE; TRIETHANOLAMINE; .ALPHA.-TOCOPHEROL ACETATE; LECITHIN, SOYBEAN; WATER; PROPYLENE GLYCOL

82929-011

Active ingredient

Lidocaine 5%

Purpose

Anorectal (Hemorrhoidal)

Uses

For temporary relief of local itching and discomfort Associated with anorectal disorders

Warnings

For external use only.
If condition worsens or does not improve within 7 days, consult a doctor.

Do not exceed the recommended daily dosage unless directed by a doctor.

Do not put this product into the rectum by using fingers or any mechanical device or applicator.
Certain persons can develop allergic reactions to ingredients in this product. If the symptom being treated does not subside or if redness, irritation, swelling, pain, or other symptoms develop or increase, discontinue use and consult a doctor.

Keep out of reach of children

if swallowed get medical help or contact a Poison Control Center right away.

Directions

Adults: When practical, cleanse the affected area with mild soap and warm water and rinse thoroughly. Gently dry by patting or blotting with toilet tissue or a soft cloth before application of this product.
Children under 12 years of age: consult a doctor.
Apply externally to the affected area. Apply to the affected area up to 6 times daily.

Inactive ingredients

Aloe barbadebsis lesf juice (Aloe vera), Water, Lecithin (Soybean), Propylene Glycol, Tocopheryl Acetate, Carbomer, Triethanolamine

Other Information

Store at room temperature (59-86 *F/15-30℃).
Keep away from direct sunlight or heat.
Keep out the reach of children. The package is child-resistant.
Do not use this product if seal is broken or missing
In case of accidental overdose and ingestion, call a doctor immediately.